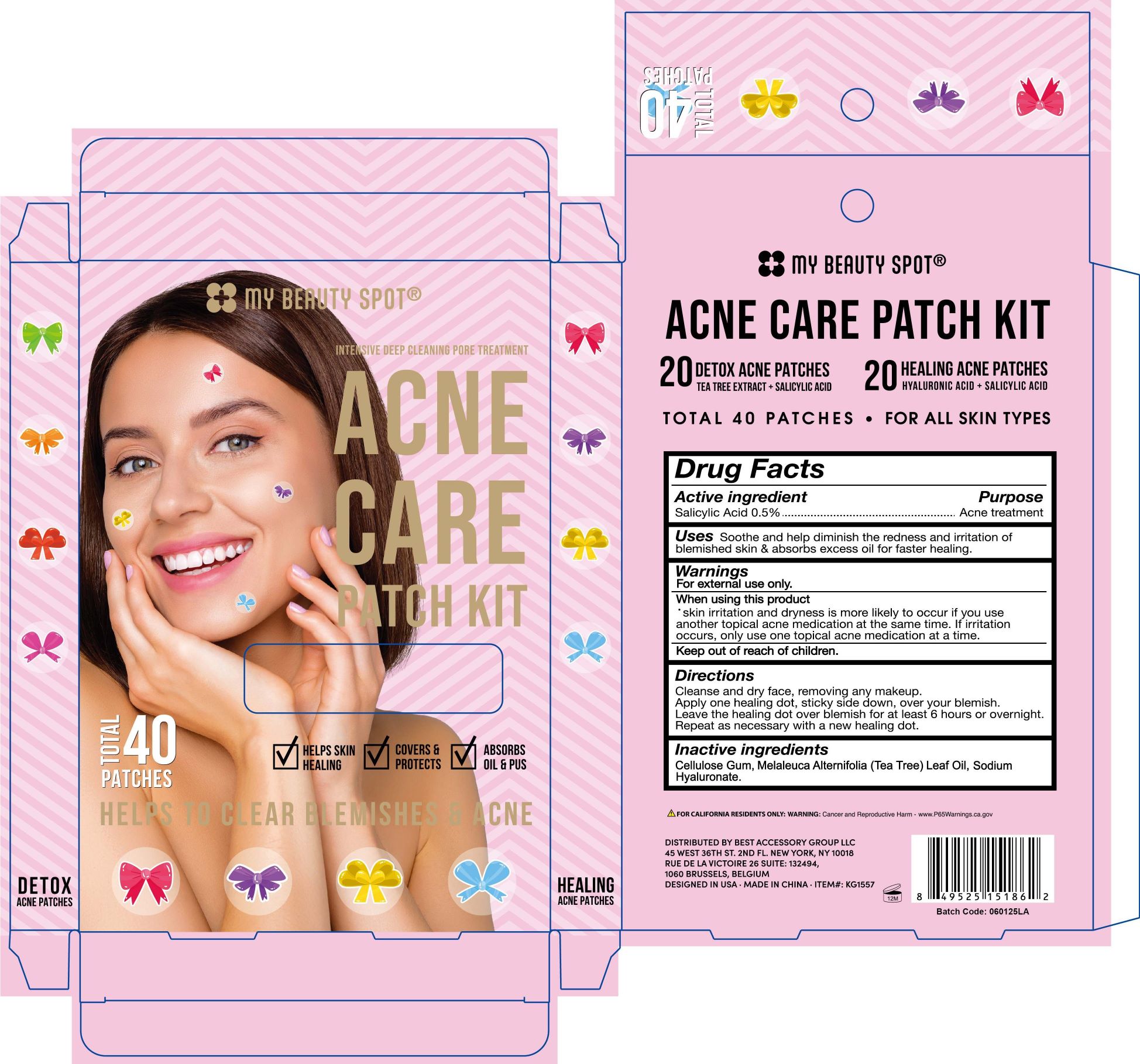 DRUG LABEL: Acne Buster
NDC: 78882-402 | Form: PATCH
Manufacturer: Hangzhou Bo Clean Hygiene Products Co., Ltd
Category: otc | Type: HUMAN OTC DRUG LABEL
Date: 20250709

ACTIVE INGREDIENTS: SALICYLIC ACID 5 mg/1000 mg
INACTIVE INGREDIENTS: CARBOXYMETHYLCELLULOSE SODIUM; MELALEUCA ALTERNIFOLIA (TEA TREE) LEAF OIL; SODIUM HYALURONATE

Acne Buster *40

Active ingredient

Salicylic Acid, 0.5%. Purpose: Acne treatment

Purpose

Acne treatment

Uses

Soothe and help diminish the redness and irritation of blemished skin & absorbs excess oil for faster healing.

Warnings

For external use only.

When using this product

- skin irritation and dryness is more likely to occur if you use another topical acne medication at the same time. If irritation occurs, only use one topical acne medication at a time.

Keep out of reach of children.

Directions

Cleanse and dry face, removing any makeup.

Apply one healing dot, sticky side down, over your blemish.

Leave the healing dot over blemish for at least 6 hours or overnight.

Repeat as necessary with a new healing dot.

Inactive ingredients

Cellulose Gum, Melaleuca Alternifolia (Tea Tree) Leaf Oil, Sodium Hyaluronate.